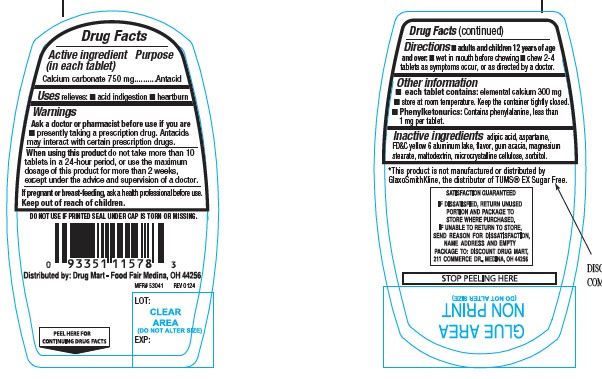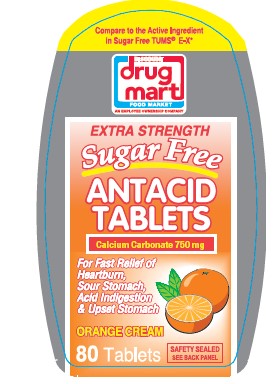 DRUG LABEL: Extra Strength sugar free Antacid
NDC: 53943-181 | Form: TABLET, CHEWABLE
Manufacturer: Discount Drug Mart, Inc
Category: otc | Type: Human OTC Drug Label
Date: 20250225

ACTIVE INGREDIENTS: CALCIUM CARBONATE 750 mg/1 1
INACTIVE INGREDIENTS: ADIPIC ACID; ASPARTAME; MAGNESIUM STEARATE; MALTODEXTRIN; FD&C YELLOW NO. 6; MICROCRYSTALLINE CELLULOSE; SORBITOL; ACACIA

Extra Strength sugar free Antacid

ACTIVE INGREDIENT (in each tablet)

Calcium carbonate 750 mg

PURPOSE

Antacid

USE(S)

relieves:

- acid indigestion
- heartburn

WARNINGS

.

ASK A DOCTOR OR PHARMACIST BEFORE USE IF YOU ARE

- presently taking a prescription drug. Antacids may interact with certain prescription drugs.

WHEN USING THIS PRODUCT

do not take more than 10 tablets in a 24-hour period, or use the maximum dosage of this product for more than 2 weeks, except under the advice and supervision of a doctor.

IF PREGNANT OR/BREASTFEEDING,

ask a health professional before use.

KEEP OUT OF REACH OF CHILDREN

.

DIRECTIONS

- adults and children 12 years of age and over: wet in mouth before chewing
- chew 2-4 tablets as symptoms occur, or as directed by a doctor.

OTHER INFORMATION

- each tablet contains: elemental calcium 300 mg
- store at room temperature. Keep the container tightly closed.
- Phenylketonurics: Contains phenylalanine, less than 1 mg per tablet.

INACTIVE INGREDIENTS

adipic acid, aspartame, FD&C yellow 6 aluminum lake, flavor, gum acacia, magnesium stearate, maltodextrin, microcrystalline cellulose, sorbitol.

PRINCIPAL DISPLAY PANEL

Compare to the Active Ingredient in Sugar Free Tums® E-X*
DISCOUNT drug mart FOOD MARKET

EXTRA STRENGTH sugar free

ANTACID TABLETS
Calcium Carbonate 750 mg
For Fast Relief of:

Heartburn,

Sour Stomach,

Acid indigestion

& Upset Stomach

ORANGE CREAM
80 Tablets

SAFETY SEALED
SEE BACK PANEL